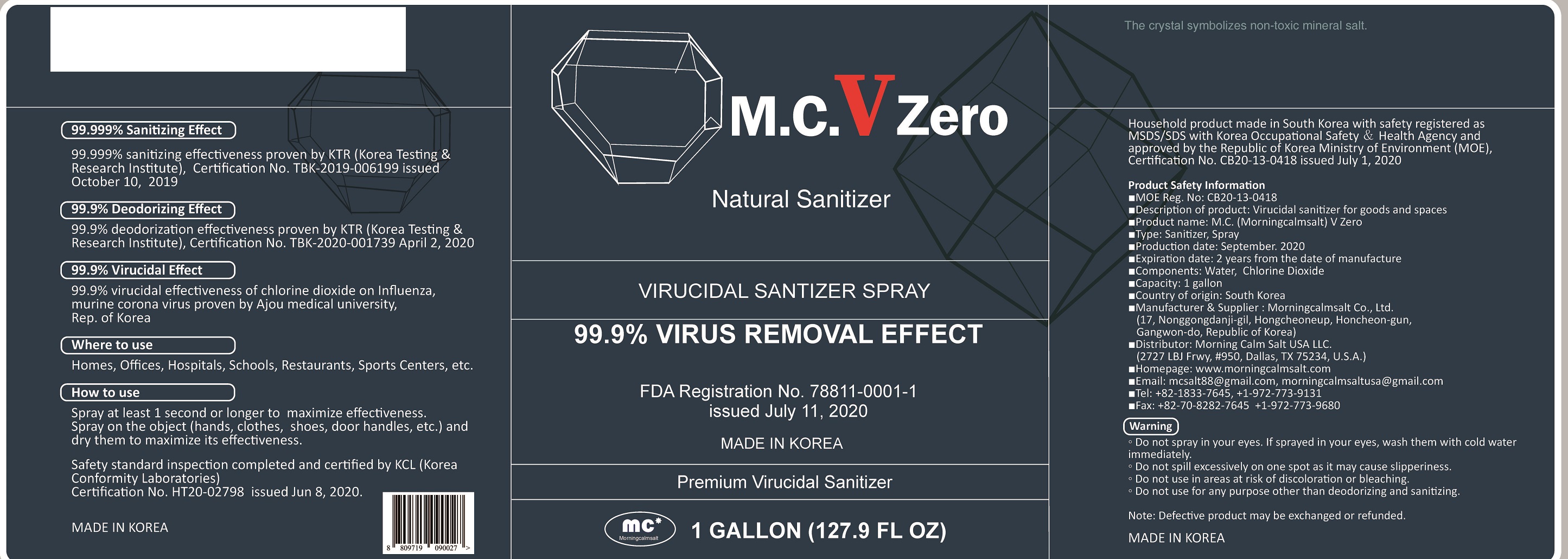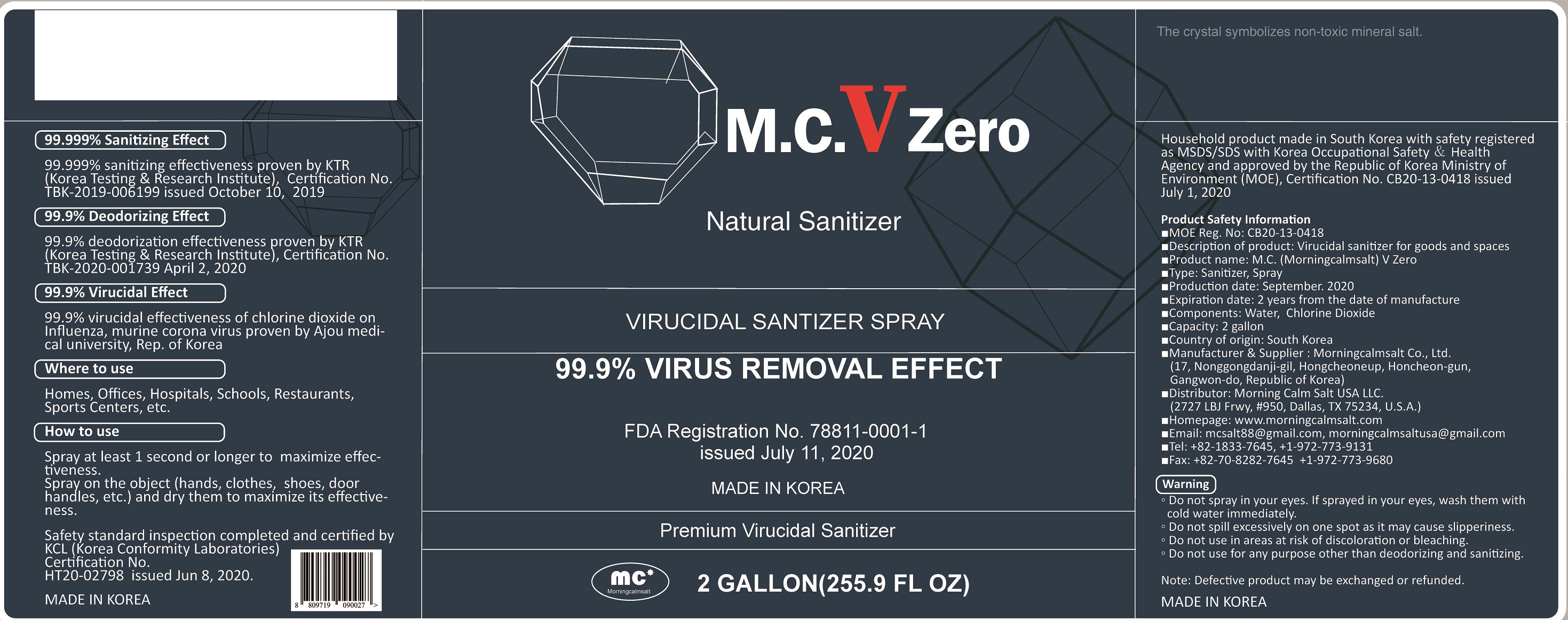 DRUG LABEL: M.C. (Morningcalm) V Zero
NDC: 78811-0002 | Form: LIQUID
Manufacturer: Morningcalmsalt Co., Ltd.
Category: otc | Type: HUMAN OTC DRUG LABEL
Date: 20201006

ACTIVE INGREDIENTS: CHLORINE DIOXIDE 0.3 g/100 mL
INACTIVE INGREDIENTS: WATER

Active Ingredient(s)

chlorine dioxide

Purpose

Anti-virus mineral deodorant

Use

Spray Morningcalm V Zero at the place used as
high as possible for maximum effect (it is effective
to allow more than 1 second of time to pass).
• Spray Morningcalm V Zero on object (mask, clothes,
shoes, etc.) and dry it to increase the effect

Warnings

Do not use Morningcalm V Zero for any purpose other
than deodorant. If Morningcalm V Zero is sprayed
in your face or eyes, wash them with cold water
immediately.
• Do not spill Morningcalm V Zero excessively on
one spot as it may cause slipperiness.
• Do not use Morningcalm V Zero in areas
at risk of discoloration or
bleaching.

 Keep out of reach of children. If swallowed, get medical help or contact a Poison Control Center immediately.

Directions

for external use only

INACTIVE INGREDIENT

Bentonite, Sericite, Sulfur, Molybdate , Calcium , Chitosan, Iodine, Purified water, etc.